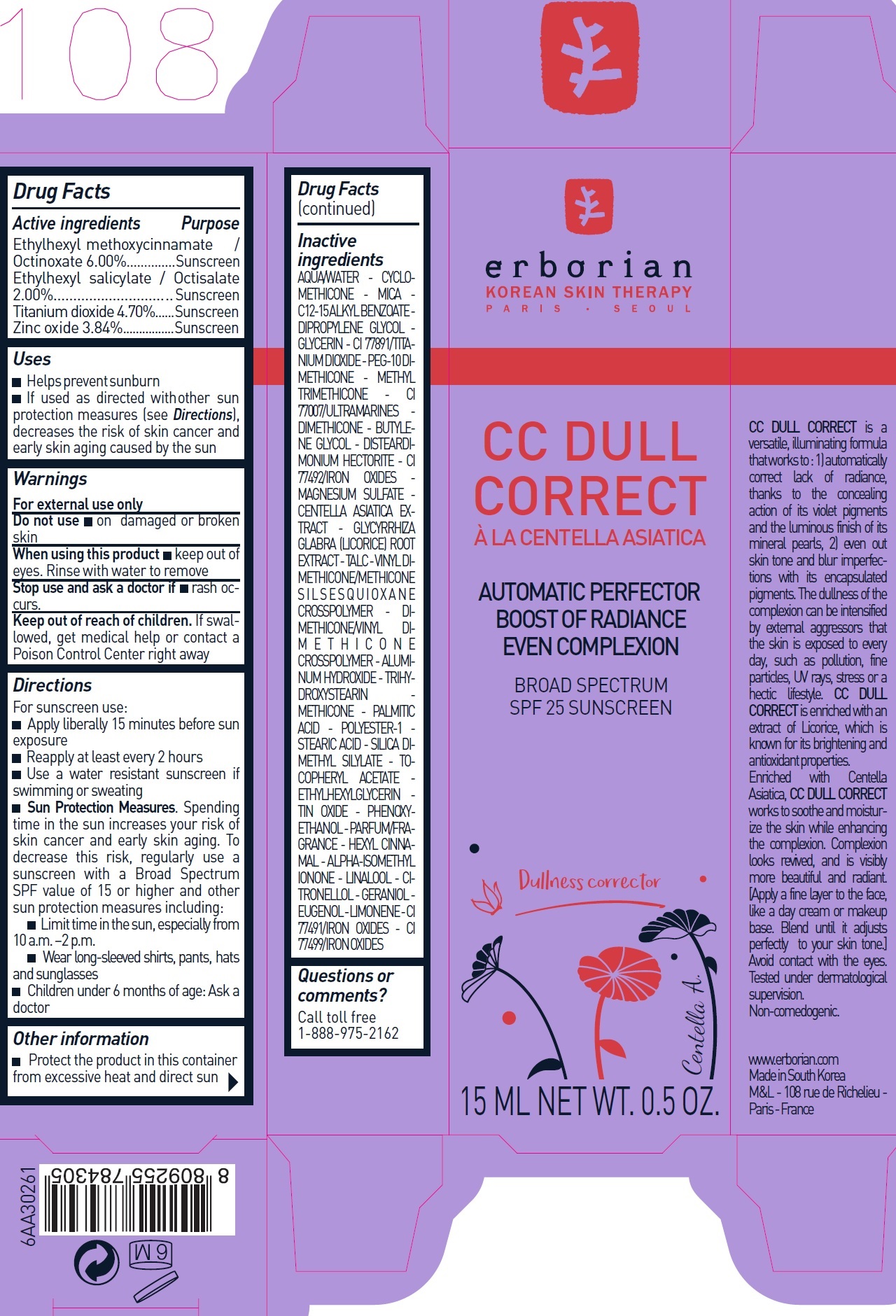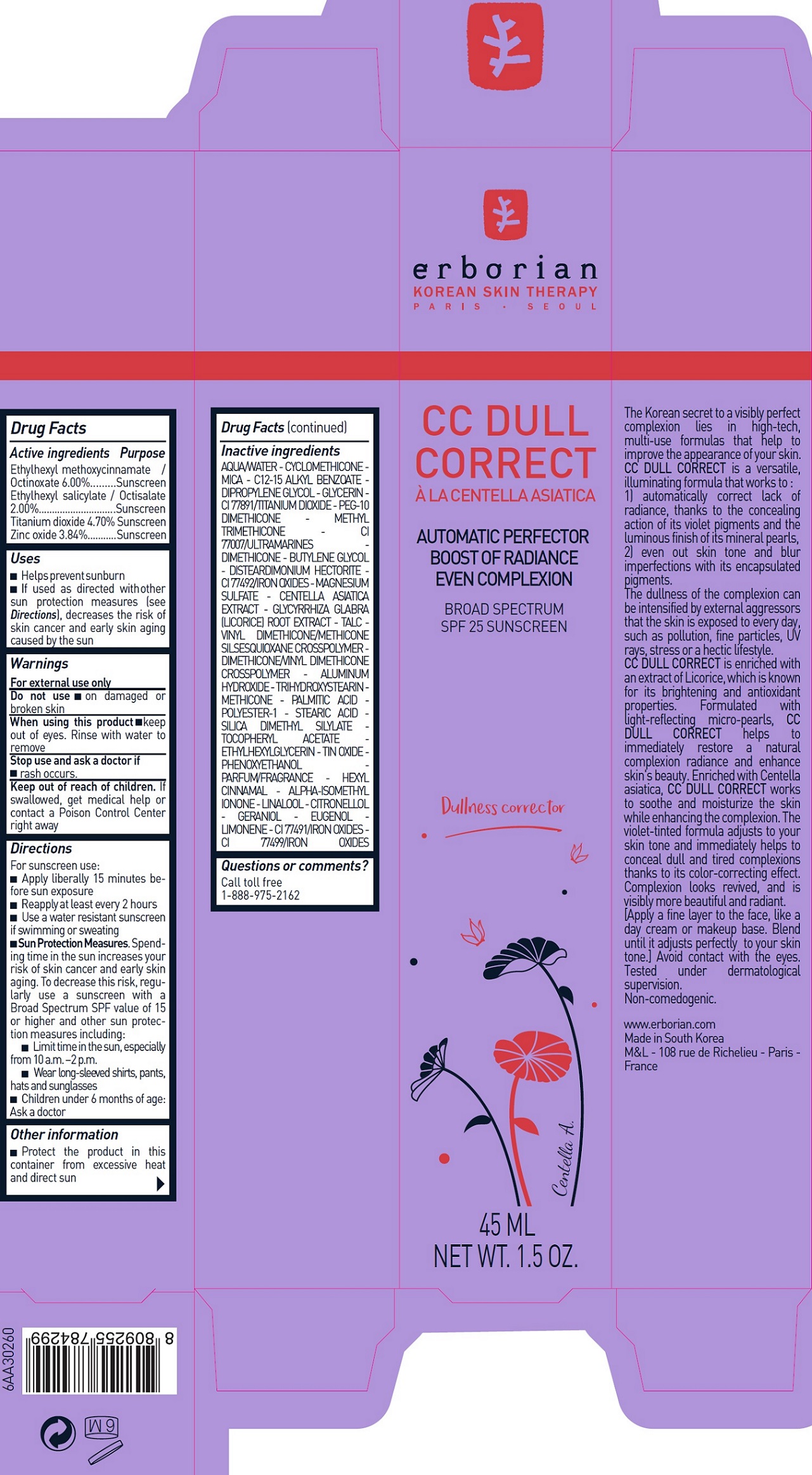 DRUG LABEL: Erborian CC Dull Correct SPF25
NDC: 10345-914 | Form: CREAM
Manufacturer: LABORATOIRES M&L
Category: otc | Type: HUMAN OTC DRUG LABEL
Date: 20231209

ACTIVE INGREDIENTS: OCTINOXATE 60 mg/1 mL; OCTISALATE 20 mg/1 mL; TITANIUM DIOXIDE 47 mg/1 mL; ZINC OXIDE 38.4 mg/1 mL
INACTIVE INGREDIENTS: WATER; CYCLOMETHICONE; MICA; DIPROPYLENE GLYCOL; GLYCERIN; PEG-10 DIMETHICONE (600 CST); METHYL TRIMETHICONE; ULTRAMARINE BLUE; DIMETHICONE; BUTYLENE GLYCOL; DISTEARDIMONIUM HECTORITE; FERRIC OXIDE YELLOW; MAGNESIUM SULFATE, UNSPECIFIED FORM; CENTELLA ASIATICA; GLYCYRRHIZA GLABRA; TALC; ALUMINUM HYDROXIDE; TRIHYDROXYSTEARIN; METHICONE (20 CST); PALMITIC ACID; STEARIC ACID; SILICA DIMETHYL SILYLATE; .ALPHA.-TOCOPHEROL ACETATE; ETHYLHEXYLGLYCERIN; STANNIC OXIDE; PHENOXYETHANOL; .ALPHA.-HEXYLCINNAMALDEHYDE; ISOMETHYL-.ALPHA.-IONONE; GERANIOL; EUGENOL; FERRIC OXIDE RED; FERROSOFERRIC OXIDE

Erborian – CC Dull Correct SPF25

Active ingredients

Ethylhexyl methoxycinnamate / Octinoxate 6.00%

Ethylhexyl salicylate / Octisalate 2.00%

Titanium dioxide 4.70%

Zinc oxide 3.84%

Purpose

Sunscreen

Uses

- Helps prevent sunburn
- If used as directed with other sun protection measures (see Directions), decreases the risk of skin cancer and early skin aging caused by the sun

Warnings

For external use only

Do not use

- on damaged or broken skin

When using this product

- keep out of eyes. Rinse with water to remove

Stop use and ask a doctor if

- rash occurs.

Keep out of reach of children.

If swallowed, get medical help or contact a Poison Control Center right away

Directions

For sunscreen use:

- Apply liberally 15 minutes before sun exposure
- Reapply at least every 2 hours
- Use a water resistant sunscreen if swimming or sweating
- Spending time in the sun increases your risk of skin cancer and early skin aging. To decrease this risk, regularly use a sunscreen with a Broad Spectrum SPF value of 15 or higher and other sun protection measures including: Sun Protection Measures.
- Limit time in the sun, especially from 10 a.m. –2 p.m.
- Wear long-sleeved shirts, pants, hats and sunglasses
- Children under 6 months of age: Ask a doctor

Other information

Protect the product in this container from excessive heat and direct sun

Inactive ingredients

AQUA/WATER - CYCLOMETHICONE - MICA - C12-15 ALKYL BENZOATE - DIPROPYLENE GLYCOL - GLYCERIN - CI 77891/TITANIUM DIOXIDE - PEG-10 DIMETHICONE - METHYL TRIMETHICONE - CI 77007/ULTRAMARINES - DIMETHICONE - BUTYLENE GLYCOL - DISTEARDIMONIUM HECTORITE - CI 77492/IRON OXIDES - MAGNESIUM SULFATE - CENTELLA ASIATICA EXTRACT - GLYCYRRHIZA GLABRA (LICORICE) ROOT EXTRACT - TALC - VINYL DIMETHICONE/METHICONE SILSESQUIOXANE CROSSPOLYMER - DIMETHICONE/ VINYL DIM E T H I C O N E CROSSPOLYMER - ALUMINUM HYDROXIDE - TRIHYDROXYSTEARIN - METHICONE - PALMITIC ACID - POLYESTER-1 - STEARIC ACID - SILICA DIMETHYL SILYLATE - TOCOPHERYL ACETATE - ETHYLHEXYLGLYCERIN - TIN OXIDE - PHENOXYETHANOL - PARFUM/FRAGRANCE - HEXYL CINNAMAL- ALPHA-ISOMETHYL IONONE - LINALOOL - CITRONELLOL - GERANIOL - EUGENOL - LIMONENE - CI 77491/IRON OXIDES - CI 77499/IRON OXIDES

Questions or comments?

Call toll free 1-888-975-2162